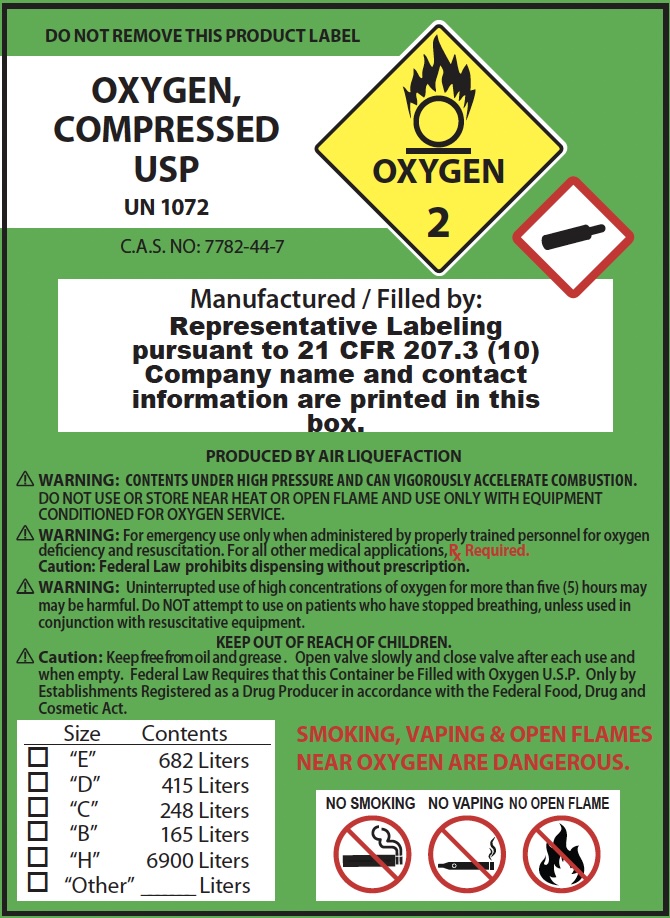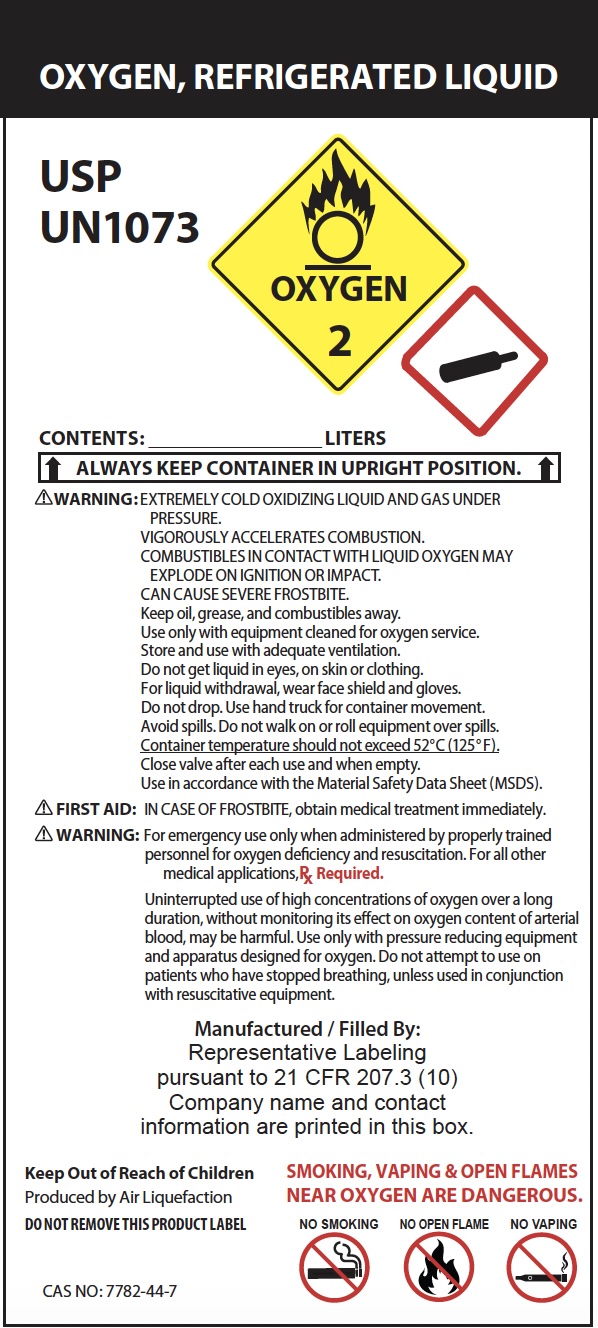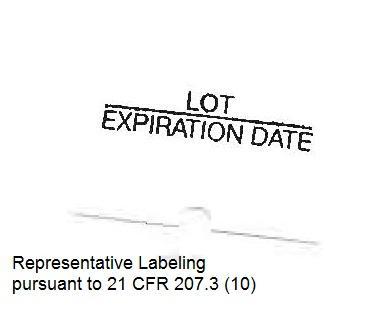 DRUG LABEL: Oxygen
NDC: 70672-001 | Form: GAS
Manufacturer: Dade Medical, Inc. dba Integrated Home Care	
Category: prescription | Type: HUMAN PRESCRIPTION DRUG LABEL
Date: 20251014

ACTIVE INGREDIENTS: OXYGEN 99 L/100 L

Oxygen

Principal for Oxygen Product

DO NOT REMOVE THIS PRODUCT LABEL

OXYGEN, COMPRESSED USP

UN 1072

C.A.S. NO: 7782-44-7

Manufactured / Filled by:

PRODUCED BY AIR LIQUEFACTION

WARNING: CONTENTS UNDER HIGH PRESSURE AND CAN VIGOROUSLY ACCELERATE COMBUSTION.
DO NOT USE OR STORE NEAR HEAT OR OPEN FLAME AND USE ONLY WITH EQUIPMENT CONDITIONED FOR OXYGEN SERVICE.
WARNING: For emergency use only when administered by properly trained personnel for oxygen deficiency and resuscitation. For all other medical applications, Rx Required.
Caution: Federal Law prohibits dispensing without prescription.
WARNING: Uninterrupted use of high concentrations of oxygen for more than five (5) hours may be harmful. Do NOT attempt to use on patients who have stopped breathing, unless used in conjunction with resuscitative equipment.
KEEP OUT OF REACH OF CHILDREN.
Caution: Keep free from oil and grease. Open valve slowly and close valve after each use and
when empty. Federal Law Requires that this Container be Filled with Oxygen U.S.P. Only by Establishments Registered as a Drug Producer in accordance with the Federal Food, Drug and
Cosmetic Act.
SMOKING, VAPING & OPEN FLAMES
NEAR OXYGEN ARE DANGEROUS.
NO SMOKING NO VAPING NO OPEN FLAME

OXYGEN, REFRIGERATED LIQUID
USP

UN1073

CONTENTS: _____________________________ LITERS

A LWAYS KEEP CONTAINER IN UPRIGHT POSITION.

WARNING: EXTREMELY COLD OXIDIZING LIQUID AND GAS UNDE R

PRESSURE.

VIGOROUSLY ACCELERATES COMBUSTION.

COMBUSTIBLES IN CONTACT WITH LIQUID OXYGEN MAY

EXPLODE ON IGNITION OR IMPACT.

CAN CAUSE SEVERE FROSTBITE.

Keep oil, grease, and combustibles away.

Use only with equipment cleaned for oxygen service.

Store and use with adequate ventilation.

Do not get liquid in eyes, on skin or clothing.

For liquid withdrawal, wear face shield and gloves.

Do not drop. Use hand truck for container movement.

Avoid spills. Do not walk on or roll equipment over spills.

Container temperature should not exceed 52°C (125°F).

Close valve after each use and when empty.

Use in accordance with the Material Safety Data Sheet (MSDS).

FIRST AID: IN CASE OF FROSTBITE, obtain medical treatment immediately.

WARNING: For emergency use only when administered by properly trained

personnel for oxygen deficiency and resuscitation. For all other

medical applications, Rx Required.

Uninterrupted use of high concentrations of oxygen over a long

duration, without monitoring its effect on oxygen content of arterial

blood, may be harmful. Use only with pressure reducing equipment

and apparatus designed for oxygen. Do not attempt to use on

patients who have stopped breathing, unless used in conjunction

with resuscitative equipment.

Keep Out of Reach of Children

Produced by Air Liquefaction

DO NOT REMOVE THIS PRODUCT LABEL

SMOKING, VAPING & OPEN FLAMES

NEAR OXYGEN ARE DANGEROUS.

NO SMOKING NO OPEN FLAME NO VAPING